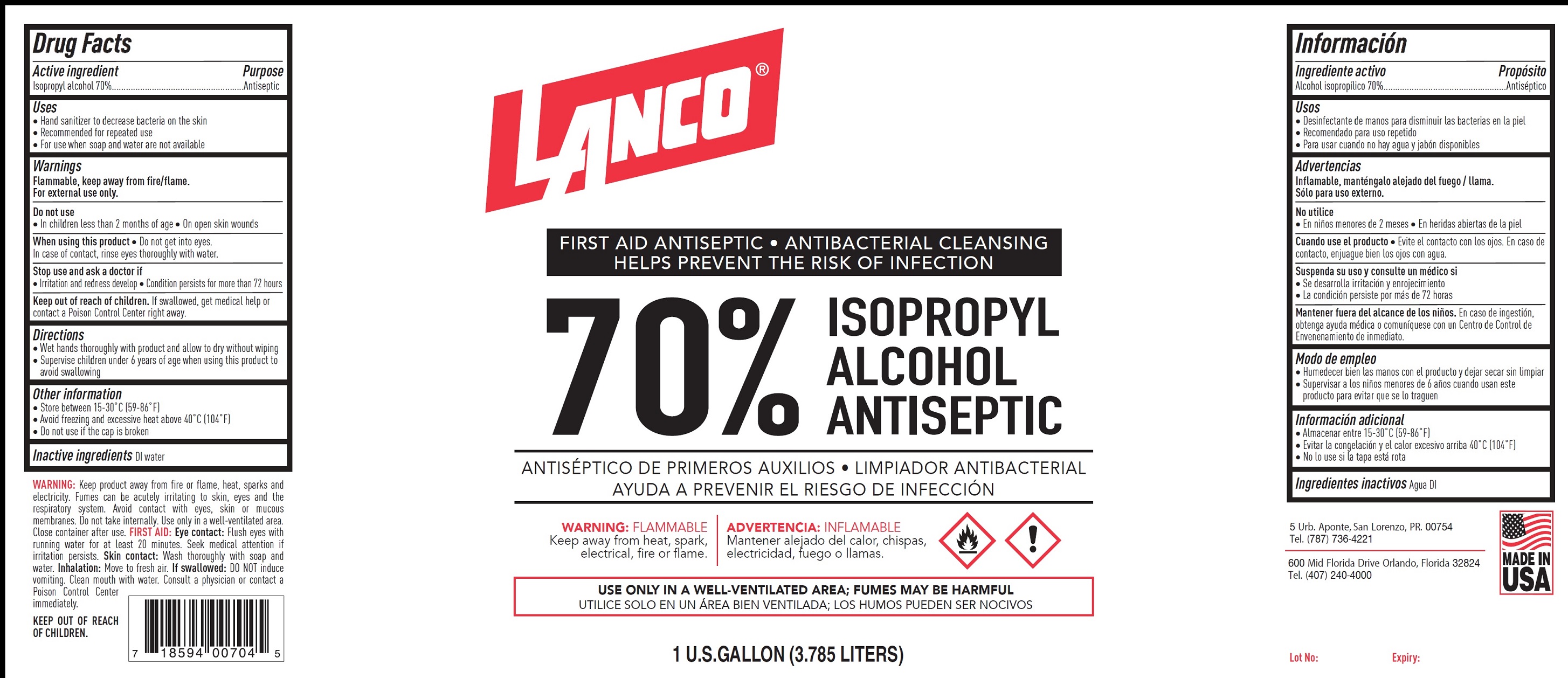 DRUG LABEL: Lanco 70 Isopropyl Alcohol Antiseptic
NDC: 80522-000 | Form: LIQUID
Manufacturer: Lanco Manufacturing, Corp.
Category: otc | Type: HUMAN OTC DRUG LABEL
Date: 20201209

ACTIVE INGREDIENTS: ISOPROPYL ALCOHOL 0.7 mL/1 mL
INACTIVE INGREDIENTS: WATER

Lanco 70% Isopropyl Alcohol Antiseptic

Active ingredient

Isopropyl alcohol 70%

Purpose

Antiseptic

Uses

- Hand sanitizer to decrease bacteria on the skin
- Recommended for repeated use
- For use when soap and water are not available

Warnings

Flammable, keep away from fire/flame.
For external use only.

Do not use

- In children less than 2 months of age
- On open skin wounds

When using this product

- Do not get into eyes. In case of contact, rinse eyes thoroughly with water

Stop use and ask a doctor if

- Irritation and redness develop
- Condition persists for more than 72 hours

Keep out of reach of children.

If swallowed, get medical help or contact a Poison Control Center right away.

Directions

- Wet hands thoroughly with product and allow to dry without wiping
- Supervise children under 6 years of age when using this product to avoid swallowing

Other information

- Store between 15-30° C [59-86°F]
- Avoid freezing and excessive heat above 40° C [104°F]
- Do not use if the cap is broken

Inactive ingredients

DI water